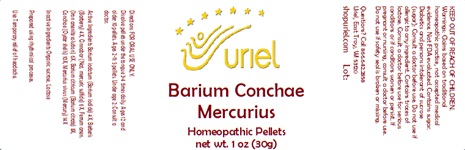 DRUG LABEL: Barium Conchae Mercurius
NDC: 48951-2147 | Form: PELLET
Manufacturer: Uriel Pharmacy Inc.
Category: homeopathic | Type: HUMAN OTC DRUG LABEL
Date: 20241223

ACTIVE INGREDIENTS: BARIUM IODATE 4 [hp_X]/1 1; BERBERIS VULGARIS ROOT BARK 4 [hp_X]/1 1; MERCURIC SULFIDE 6 [hp_X]/1 1; FERROUS ARSENATE 6 [hp_X]/1 1; BARIUM CITRATE 8 [hp_X]/1 1; OSTREA EDULIS SHELL 10 [hp_X]/1 1; MERCURY 14 [hp_X]/1 1
INACTIVE INGREDIENTS: SUCROSE; LACTOSE

Barium Conchae Mercurius

INDICATIONS AND USAGE

Directions: FOR ORAL USE ONLY.

DOSAGE AND ADMINISTRATION

Dissolve pellets under the tongue 3-4 times daily. Ages 12 and older: 10 pellets. Ages 2-11: 5 pellets. Under age 2: Consult a doctor.

ACTIVE INGREDIENT

Active Ingredients: Barium iodatum (Barium iodide) 4X, Berberis (Barberry) 4X, Cinnabar (Nat. mercuric sulfide) 6X, Ferrum arsen. (Iron arsenite solution) 6X, Barium citricum (Barium citrate) 8X, Conchae (Oyster shells) 10X, Mercurius vivus (Mercury) 14X

Inactive Ingredients: Organic sucrose, Lactose

Prepared using rhythmical processes.

PURPOSE

Use: Temporary relief of sore throat.

KEEP OUT OF REACH OF CHILDREN.

WARNINGS

Warnings: Claims based on traditional homeopathic practice, not accepted medical evidence. Not FDA evaluated. Contains sugar. Diabetics and persons intolerant of sucrose (sugar): Consult a doctor before use. Do not use if allergic to any ingredient. Contains traces of lactose. Consult a doctor before use for serious conditions or if conditions worsen or persist. If pregnant or nursing, consult a doctor before use. Do not use if safety seal is broken or missing.

QUESTIONS

Questions? Call 866.642.2858 Uriel, East Troy, WI 53120 shopuriel.com Lot: